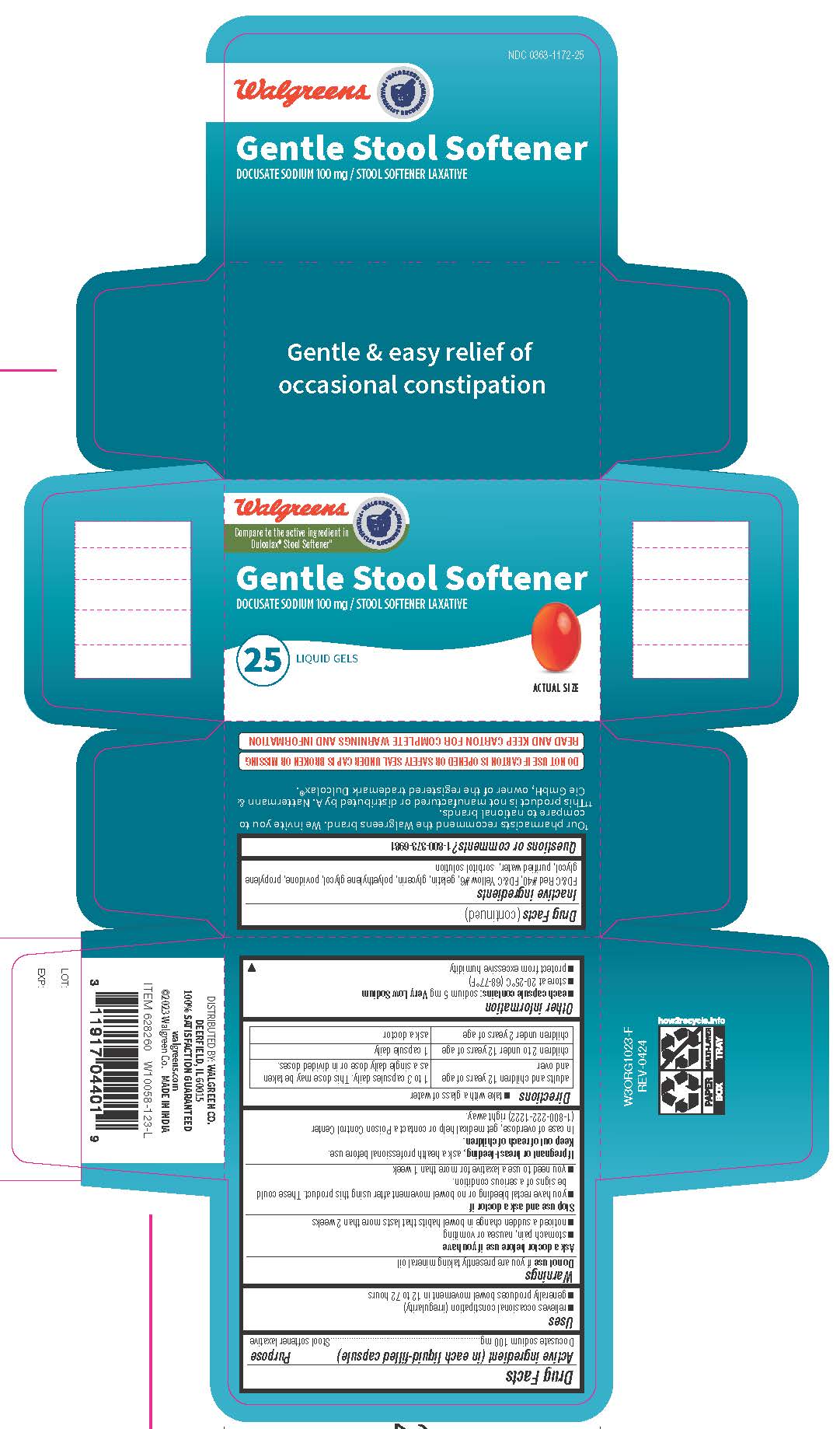 DRUG LABEL: Gentle Stool Softener
NDC: 0363-1172 | Form: CAPSULE, LIQUID FILLED
Manufacturer: WALGREEN COMPANY
Category: otc | Type: HUMAN OTC DRUG LABEL
Date: 20251031

ACTIVE INGREDIENTS: DOCUSATE SODIUM 100 mg/1 1
INACTIVE INGREDIENTS: FD&C RED NO. 40; FD&C YELLOW NO. 6; GELATIN; GLYCERIN; POLYETHYLENE GLYCOL 400; POVIDONE; PROPYLENE GLYCOL; WATER; SORBITOL SOLUTION

Gentle Stool Softener

Drug Facts

Active ingredient (in each liquid-filled capsule)

Docusate Sodium 100 mg

Purpose

Stool Softner laxative

Uses

- relieves of occasional constipation (irregularity)
- generally produces a bowel movement within 12 to 72 hours

Warnings

Do not use if you are presently taking mineral o il

Ask a doctor before use if you have

- stomach pain, nausea or vomittiong
- noticed a sudden change in bowel habits that lasts more than 2 weeks

Stop use and ask a doctor if you

- you have rectal bleeding ot no bowel movement after using this product. These could be signs of a serious condition.
- yo need to use laxative for more than 1 week

PREGNANCY OR BREAST FEEDING

If pregnant or breast-feeding, ask a health professional before use

Keep out of reach of children. In case of overdose, get medical help or contact a Poison Control Center right away.1(800)222-1222 righ away.

Directions

- take with a glass of water

Adults and children 12 years of age and over | take 1 to 3 capsules daily. This dose may be taken as asingle daily dose or ib divided doses.
Children 2 to under 12 years of age | 1 capsule daily.
Children under 2 years of age | Ask a doctor

Other information

- each capsule contains: sodium 5 mg Very Low Sodium
- Store at room temperature 20-25°C (68-77°F)
- protect from excessive humidity

Inactive ingredients

FD&C Red #40, FD&C Yellow #6, gelatin, glycerin, polyethylene glycol, povidone, propylene
glycol, purified water, sorbitol solution.

Questions or comments?

1-800-373-6981

Distributed by: Walgreen co.
200 Wilmot rd., Deerfield, IL 60015

PRINCIPAL DISPLAY PANEL

Compare to Dulcolax ® Stool Softener active ingredient *

GENTLE STOOL SOFTENER

DOCUSATE SODIUM 100 mg / STOOL SOFTENER LAXATIVE

25 LIQUID GELS